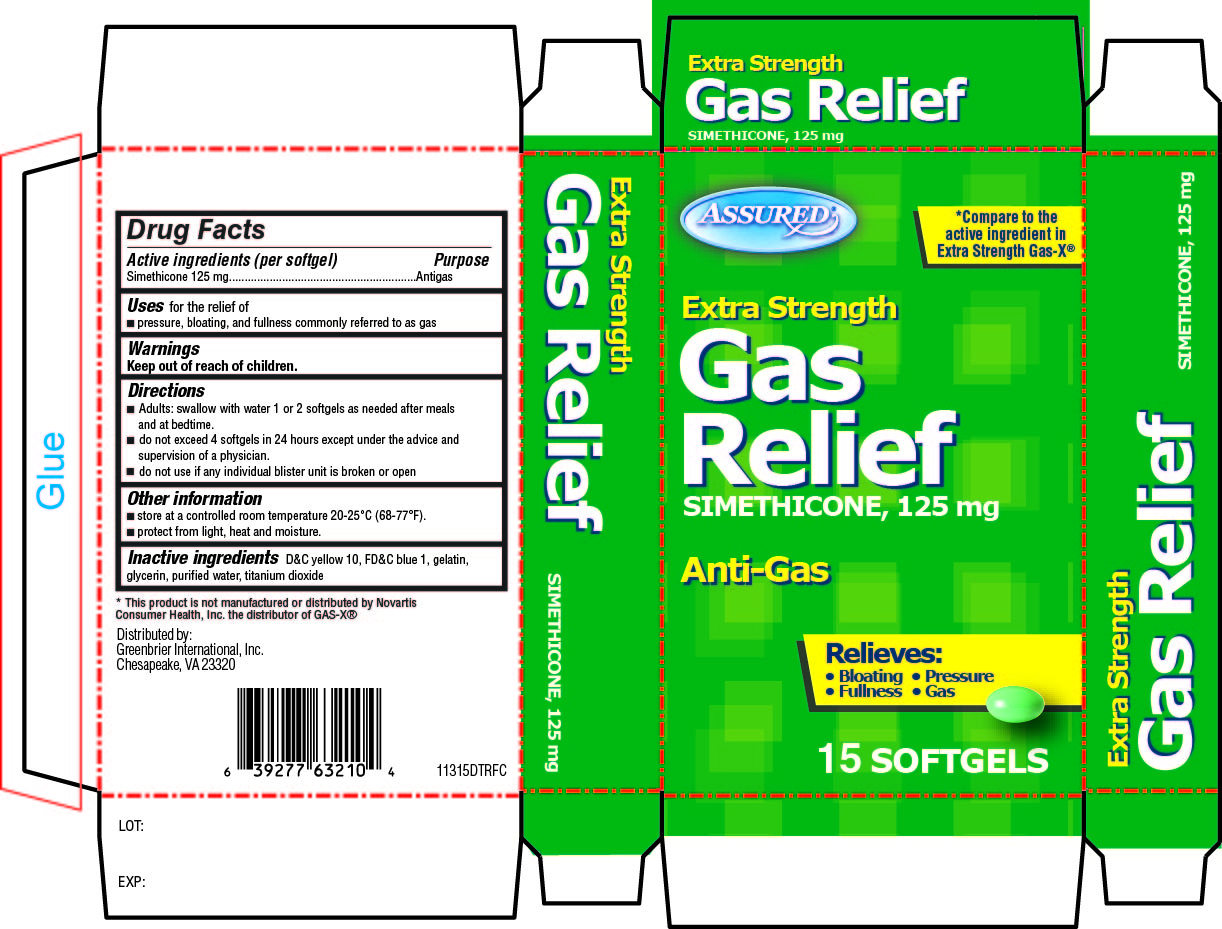 DRUG LABEL: Assured Gas Relief Extra Strength
NDC: 33992-0113 | Form: CAPSULE, LIQUID FILLED
Manufacturer: Greenbrier International, Inc.
Category: otc | Type: HUMAN OTC DRUG LABEL
Date: 20130114

ACTIVE INGREDIENTS: DIMETHICONE 125 mg/1 1
INACTIVE INGREDIENTS: D&C YELLOW NO. 10; FD&C BLUE NO. 1; GELATIN; GLYCERIN; WATER; TITANIUM DIOXIDE

Assured Gas Relief Drug Facts

Active ingredient (in each softgel)

Simethicone 125 mg

Purpose

Antigas

Uses

for the relief of

- pressure, bloating, and fullness commonly referred to as gas

Directions

- Adults: swallow with water 1 or 2 softgels as needed after meals and at bedtime
- do not exceed 4 softgels in 24 hours except under the advice and supervision of a physician
- do not use if any individual blister unit is broken or missing

Other information

- store at controlled room temperature 20°-25°C (68-77°F)
- protect from light, heat and moisture

Inactive ingredients

D&C yellow 10, FD&C blue 1, gelatin, glycerin, purified water, titanium dioxide

Principal Display Panel

Compare to active ingredient in Extra Strength Gas-X®

Extra Strength

Gas Relief

Simethicone 125 mg

Anti-Gas

Relieves:

Bloating, Pressure, Fullness, Gas

15 Softgels

Assured Gas Relief Extra Strength